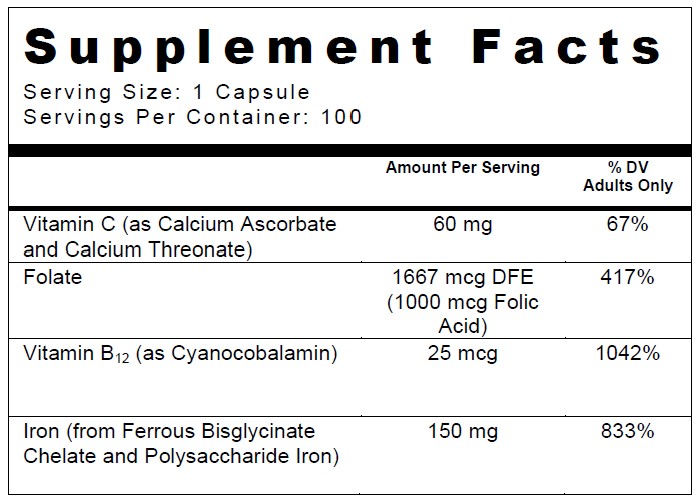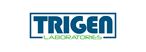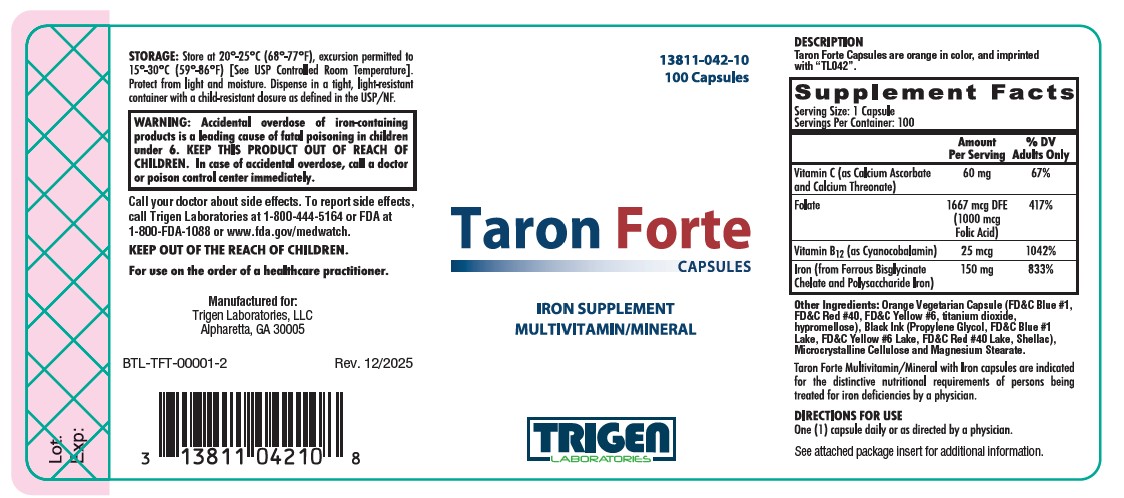 DRUG LABEL: Taron Forte
NDC: 13811-042 | Form: CAPSULE
Manufacturer: Trigen Laboratories, LLC
Category: other | Type: DIETARY SUPPLEMENT
Date: 20260105

ACTIVE INGREDIENTS: IRON 150 mg/1 1; CALCIUM ASCORBATE 60 mg/1 1; CYANOCOBALAMIN 25 ug/1 1; FOLIC ACID 1 mg/1 1
INACTIVE INGREDIENTS: CELLULOSE, MICROCRYSTALLINE; GELATIN; TITANIUM DIOXIDE; FD&C YELLOW NO. 6; FD&C RED NO. 3; MAGNESIUM STEARATE; PROPYLENE GLYCOL; FD&C BLUE NO. 1; FD&C RED NO. 40; SHELLAC

Taron Forte
Capsules

SUPPLEMENT FACTS

Other Ingredients: Orange Vegetarian Capsule (FD&C Blue #1, FD&C Red #40, FD&C Yellow #6, titanium dioxide, hypromellose), Black Ink (Propylene Glycol, FD&C Blue #1 Lake, FD&C Yellow #6 Lake, FD&C Red #40 Lake, Shellac), Microcrystalline Cellulose and Magnesium Stearate.

Taron Forte Multivitamin/Mineral with Iron capsules are indicated for the distinctive nutritional requirements of persons being treated for iron deficiencies by a physician.

CONTRAINDICATIONS

Taron Forte Capsules are contraindicated in patients with a known hypersensitivity to any of the components of this product.

Hemochromatosis and hemosiderosis are contraindications to iron therapy.

WARNINGS

WARNING: Accidental overdose of iron-containing products is a leading cause of fatal poisoning in children under 6. KEEP THIS PRODUCT OUT OF REACH OF CHILDREN. In case of accidental overdose, call a doctor or poison control center immediately.

PRECAUTIONS

General: The type of anemia and the underlying cause or causes should be determined before starting therapy with Taron Forte Capsules. Since the anemia may be a result of a systemic disturbance, such as recurrent blood loss, the underlying cause or causes should be corrected, if possible.

Folic acid alone is improper therapy in the treatment of pernicious anemia and other megaloblastic anemias where B12 is deficient.
Folic acid in doses above 0.1 mg daily may obscure pernicious anemia assessment, such that hematologic remission can occur while neurological manifestations remain progressive.

Pediatric Use: Safety and effectiveness of this product have not been established in pediatric patients.

ADVERSE REACTIONS

Adverse reactions with iron therapy may include constipation, diarrhea, nausea, vomiting, dark stools, and abdominal pain. Adverse reactions with iron therapy are usually transient. Allergic sensitization has been reported following both oral and parenteral administration of folic acid.

The clinical cause of acute iron overdosage can be variable. Initial symptoms may include: abdominal pain, nausea, vomiting, diarrhea, tarry stools, melena, hematemesis, hypotension, tachycardia, metabolic acidosis, hyperglycemia, dehydration, drowsiness, pallor, cyanosis, lassitude, seizures, shock, and coma.

DESCRIPTION

Taron Forte Capsules are orange in color, and imprinted with “TL042”.

DIRECTIONS FOR USE

One (1) capsule daily or as directed by a physician.

HOW SUPPLIED

Taron Forte Capsules are packaged in child-resistant bottles of 100 capsules.

PRODUCT CODE 13811-042-10.

STORAGE

Store at 20°-25°C (68°-77°F), excursion permitted to 15°-30°C (59°-86°F) [See USP Controlled Room Temperature]. Protect from light and moisture. Dispense in a tight, light-resistant container with a child-resistant closure as defined in the USP/NF.

KEEP OUT OF REACH OF CHILDREN.

For use on the order of a healthcare practitioner.

Call your doctor about side effects. To report side effects, call Trigen Laboratories at 1-770-509-4500 or FDA at 1-800-FDA-1088 or www.fda.gov/medwatch.

PLR-TARONFORTE-00001-3 Rev. 12/2025

Manufactured for:

Trigen Laboratories, LLC

Alpharetta, GA 30005

PRINCIPAL DISPLAY PANEL - 100 Capsule Bottle Label

13811-042-10

100 Capsules

Taron Forte
CAPSULES

TRIGEN
LABORATORIES